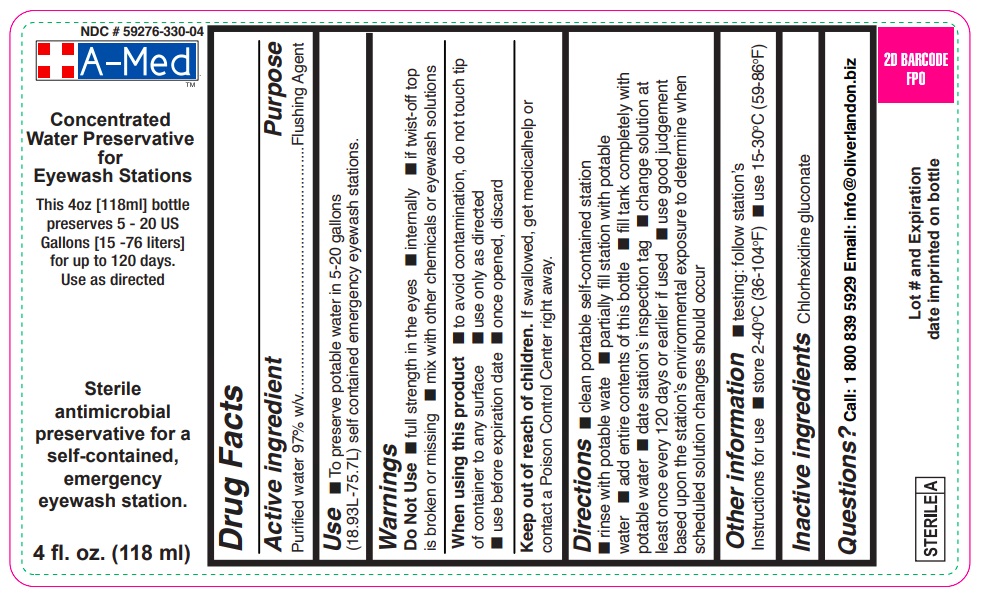 DRUG LABEL: A-Med
NDC: 59276-330 | Form: SOLUTION, CONCENTRATE
Manufacturer: Oliver Landon Intl Inc.
Category: otc | Type: HUMAN OTC DRUG LABEL
Date: 20220301

ACTIVE INGREDIENTS: WATER 97 mL/100 mL
INACTIVE INGREDIENTS: CHLORHEXIDINE GLUCONATE

A-Med Wash First Aid Eye Rinse

Drug Facts

Active ingredient

Purified water USP 97% W/V

Purpose

Eyewash

INDICATIONS AND USAGE

Use for flushing the eye to remove loose foreign material.

Warnings

For external use only

Do not use

- if solution changes color or becomes cloudy
- if you have open wounds in or near the eyes. Get medical help right away.

When using this product

- do not touch tip of container to any surface to avoid contamination
- do not reuse; once opened, discard

Stop use and ask a doctor if

- continued redness or irritation of the eye

Keep out of reach of children. If swallowed, get medical help or contact a Poison Control Center right away.

DOSAGE AND ADMINISTRATION

Directions Flush the affected eye as needed, controlling the rate of flow of solution by pressure on the bottle.

Inactive ingredients Chlorhexidine gluconate

Distributed by: Oliver Landon Intl Inc.

21 Pine Road, Belleville, St. Michael

BB 11113 Barbados

Questions or concerns:

email - info@oliverlandon.biz or call (800) 839-5929

Made in U.S.A.

Store out of direct sunlight.

PACKAGE LABEL

A-Med Wash

NDC 59276-330-04

Eyewash Additive Concentrate

Antimicrobial preservative for a self-contained, emergency eyewash station.
Preserves from 5 – 20 US Gallons (18.9 – 75.7 Liters)

4 fl. oz. (118 ml)